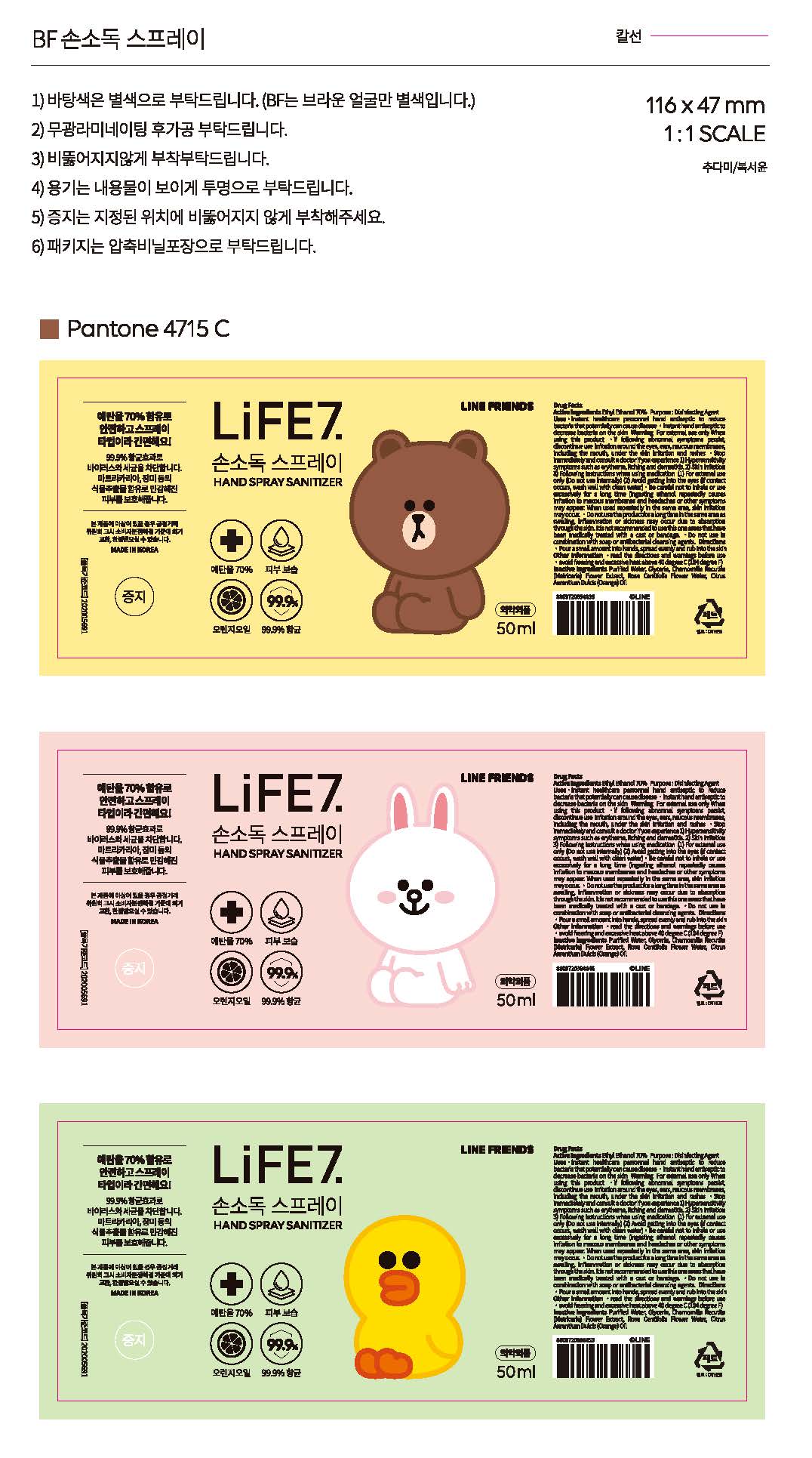 DRUG LABEL: Protect By Hand Sanitizer Water (Ethanol)
NDC: 74674-0006 | Form: LIQUID
Manufacturer: Skin n Skin Co., Ltd.
Category: otc | Type: HUMAN OTC DRUG LABEL
Date: 20200915

ACTIVE INGREDIENTS: ALCOHOL 35 mL/50 mL
INACTIVE INGREDIENTS: ORANGE OIL; WATER; GLYCERIN; CHAMOMILE; ROSA CENTIFOLIA FLOWER OIL

Skin n Skin Co., Ltd. - Protect By Hand Sanitizer Water (Ethanol)

ACTIVE INGREDIENT

Alcohol

INACTIVE INGREDIENT

PURIFIED WATER, GLYCERIN, CHAMOMILLA RECUTITA (MATRICARIA) FLOWER EXTRACT, ROSA CENTIFOLIA FLOWER WATER, CITRUS AURANTIUM DULCIS (ORANGE) OIL

PURPOSE

antiseptic

keep out of reach of the children

INDICATIONS AND USAGE

pour a small amount into hands, spread evenly and rub into the skin

WARNINGS

For external use only. Flammable. Keep away from heat or flame.

Do not use

- in children less than 2 months of age
- on open skin wounds

When using this product keep out of eyes, ears, and mouth. In case of contact with eyes, rinse thoroughly with water.

Stop use and ask a doctor if irritation or rash occurs. These may be signs of a serious condition.

Keep out of reach of children. If swallowed, get medical help or contact a Poison Control Center right away.

DOSAGE AND ADMINISTRATION

for external use only